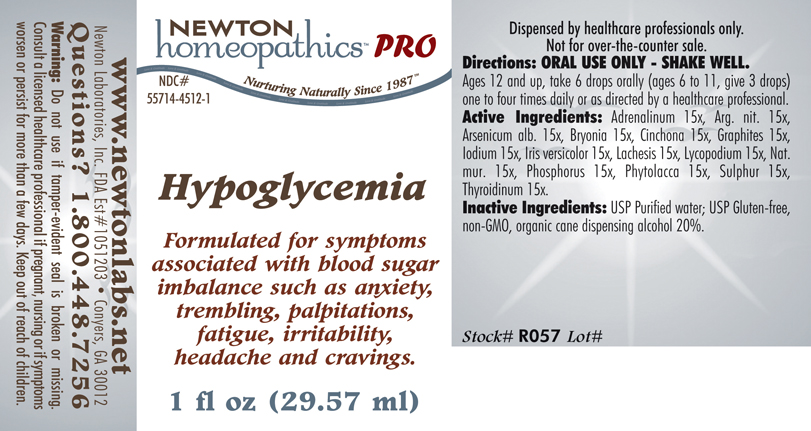 DRUG LABEL: Hypoglycemia 
NDC: 55714-4512 | Form: LIQUID
Manufacturer: Newton Laboratories, Inc.
Category: homeopathic | Type: HUMAN PRESCRIPTION DRUG LABEL
Date: 20110601

ACTIVE INGREDIENTS: Epinephrine 15 [hp_X]/1 mL; Silver Nitrate 15 [hp_X]/1 mL; Arsenic Trioxide 15 [hp_X]/1 mL; Bryonia Alba Root 15 [hp_X]/1 mL; Cinchona Officinalis Bark 15 [hp_X]/1 mL; Graphite 15 [hp_X]/1 mL; Iodine 15 [hp_X]/1 mL; Iris Versicolor Root 15 [hp_X]/1 mL; Lachesis Muta Venom 15 [hp_X]/1 mL; Lycopodium Clavatum Spore 15 [hp_X]/1 mL; Sodium Chloride 15 [hp_X]/1 mL; Phosphorus 15 [hp_X]/1 mL; Phytolacca Americana Root 15 [hp_X]/1 mL; Sulfur 15 [hp_X]/1 mL; Thyroid, Unspecified 15 [hp_X]/1 mL
INACTIVE INGREDIENTS: Alcohol

Hypoglycemia

INDICATIONS & USAGE SECTION

Hypoglycemia Formulated for symptoms associated with blood sugar imbalance such as anxiety, trembling, palpitations, fatigue, irritability, headache and cravings.

DOSAGE & ADMINISTRATION SECTION

Directions: ORAL USE ONLY - SHAKE WELL. Ages 12 and up, take 6 drops orally (ages 6 to 11, give 3 drops) one to four times daily or as directed by a healthcare professional.

ACTIVE INGREDIENT SECTION

Adrenalinum 15x, Arg. nit. 15x, Arsenicum alb. 15x, Bryonia 15x, Cinchona 15x, Graphites 15x, Iodium 15x, Iris versicolor 15x, Lachesis 15x, Lycopodium 15x, Nat.mur. 15x, Phosphorus 15x, Phytolacca 15x, Sulphur 15x, Thyroidinum 15x.

PURPOSE SECTION

Formulated for symptoms associated with blood sugar imbalance such as anxiety, trembling, palpitations, fatigue, irritability, headache and cravings.

INACTIVE INGREDIENT SECTION

Inactive Ingredients: USP Purified Water; USP Gluten-free, non-GMO, organic cane dispensing alcohol 20%.

QUESTIONS? SECTION

www.newtonlabs.net Newton Laboratories, Inc. FDA Est # 1051203 - Conyers, GA 30012
Questions? 1.800.448.7256

WARNINGS SECTION

Warning: Do not use if tamper - evident seal is broken or missing. Consult a licensed healthcare professional if pregnant, nursing or if symptoms worsen or persist for more than a few days. Keep out of reach of children.

PREGNANCY OR BREAST FEEDING SECTION

Consult a licensed healthcare professional if pregnant, nursing or if symptoms worsen or persist for more than a few days.

KEEP OUT OF REACH OF CHILDREN SECTION

Keep out of reach of children.